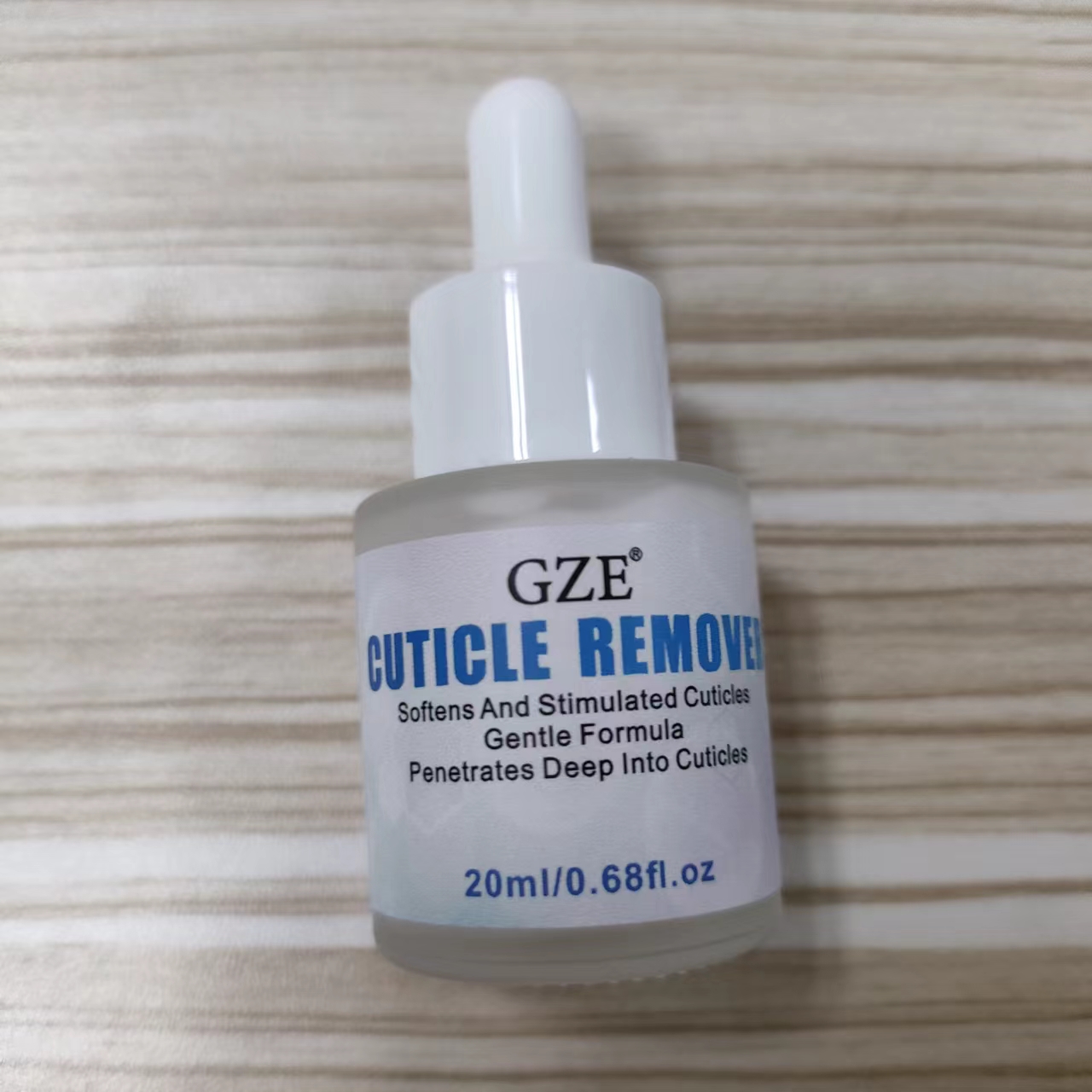 DRUG LABEL: GZE CUTICLE REMOVER
NDC: 74458-065 | Form: LIQUID
Manufacturer: Guangzhou Yilong Cosmetics Co., Ltd
Category: otc | Type: HUMAN OTC DRUG LABEL
Date: 20241109

ACTIVE INGREDIENTS: CALCIUM GLUCONATE 1.5 g/100 mL
INACTIVE INGREDIENTS: PHENOXYETHANOL; APRICOT KERNEL OIL PEG-6 ESTERS; POLYVINYL ACETATE; AQUA; TRIMETHYLOLPROPANE TRIACRYLATE; LANOLIN

GZE CUTICLE REMOVER

INDICATIONS AND USAGE

Apply around cuticles and under nails.massage nails,wait 10 seconds, push cuticles with manicure stick, wash away excess with warm water.

INACTIVE INGREDIENT

Aqua

Polyvinyl Acetate

PEG-6 Trimethylolpropane Triacrylate

Lanolin

Phenoxyethanol

Hydrogenated Apricot Kernel Oil

Parfum

ACTIVE INGREDIENT

Calcium Gluconate

WARNINGS

For external use only.

Stop use and ask a doctor if rash occurs.

Do not use on damaged or broken skin.

When using this product keep out of eyes. Rinse with water to remove.

Keep out of reach of children. If swallowed, get medical help or contact a Poison Control Center right away.

DOSAGE AND ADMINISTRATION

Apply around cuticles and under nails.massage nails,wait 10 seconds, push cuticles with manicure stick, wash away excess with warm water.